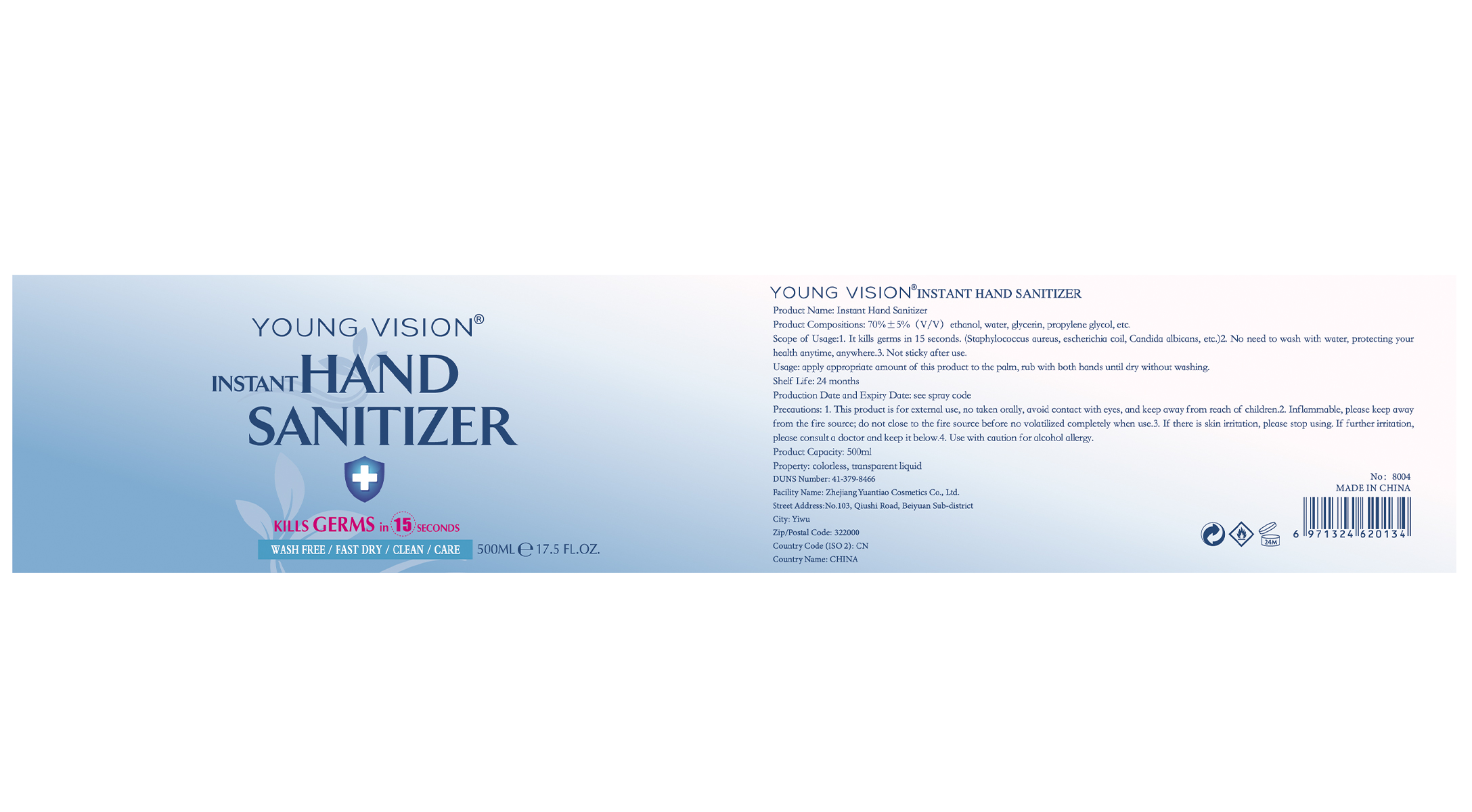 DRUG LABEL: HAND SANITIZER
NDC: 74737-2015 | Form: GEL
Manufacturer: Zhejiang Yuantiao Cosmetics Co., Ltd.
Category: otc | Type: HUMAN OTC DRUG LABEL
Date: 20200527

ACTIVE INGREDIENTS: ALCOHOL 350 mL/500 mL
INACTIVE INGREDIENTS: GLYCERIN; CARBOMER HOMOPOLYMER, UNSPECIFIED TYPE; WATER; PROPYLENE GLYCOL; AMINOMETHYLPROPANOL

YuanTiao, Hand Sanitizer, Gel, 70% Alcohol, 500 & 100mL

Active Ingredient(s)

Alcohol 70% v/v. Purpose: Antiseptic

Purpose

Antiseptic, Hand Sanitizer

Use

Hand Sanitizer to help reduce bacteria that potentially can cause disease. For use when soap and water are not available.

Warnings

Flammable. For external use only. Keep away from heat or flame.

Do not use

- on children less than 2 months of age
- on open skin wounds

When using this product keep out of eyes, ears, and mouth.

In case of contact with eyes, rinse eyes thoroughly with water.

Stop use and ask a doctor if irritation or rash occurs. These may be signs of a serious condition.

Keep out of reach of children. If swallowed, get medical help or contact a Poison Control Center right away.

Directions

- Place enough product on hands to cover all surfaces. Rub hands together until dry.
- Supervise children under 6 years of age when using this product to avoid swallowing.

Other information

- Store between 59-86℉ (15-30℃)
- Avoid freezing and excessive heat above 104℉ (40℃)

Inactive ingredients

Water, Propylene Glycol, Glycerol, Carbomer, Aminomethyl Propanol